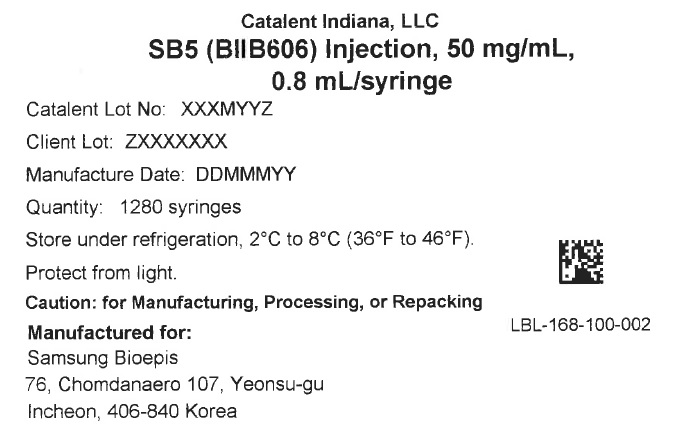 DRUG LABEL: SB5 (BIIB606)
NDC: 61434-005 | Form: INJECTION, SOLUTION
Manufacturer: Catalent Indiana, LLC
Category: prescription | Type: HUMAN PRESCRIPTION DRUG LABEL
Date: 20250813

ACTIVE INGREDIENTS: ADALIMUMAB-BWWD 40 mg/0.8 mL

168-100-300 Export